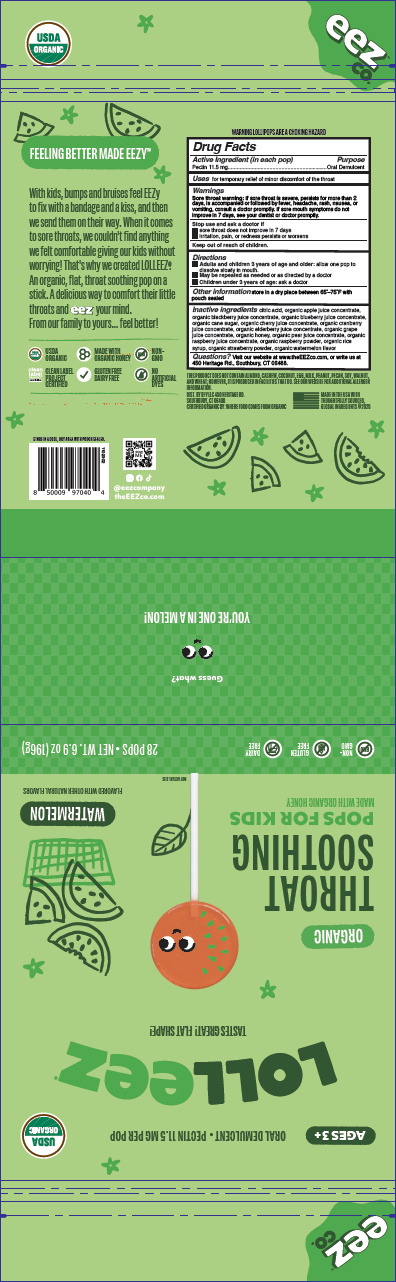 DRUG LABEL: Lolleez Watermelon
NDC: 72427-3295 | Form: LOZENGE
Manufacturer: BFY LLC
Category: otc | Type: HUMAN OTC DRUG LABEL
Date: 20260225

ACTIVE INGREDIENTS: PECTIN 11.5 mg/7 g
INACTIVE INGREDIENTS: HONEY

Lolleez Organic Watermelon 28ct

Lolleez Watermelon - Organic 28ct 3295-2

Drug Facts

Active Ingredient (in each pop)

Pectin 11.5 mg

Purpose

Oral Demulcent

Uses

for temporary relief of minor discomfort of the throat

Warnings

Sore throat warning: If sore throat is severe, persists for more than 2 days, is accompanied or followed by fever, headache, rash, nausea, or vomiting, consult a doctor promptly. If sore mouth symptoms do not improve in 7 days, see your dentist or doctor promptly.

Stop use and ask a doctor if

- sore throat does not improve in 7 days
- irritation, pain, or redness persists or worsens

Keep out of reach of children.

Keep out of reach of children

Directions

- Adults and children 3 years of age and older: allow one pop to dissolve slowly in mouth.
- May be repeated as needed or as directed by a doctor
- Children under 3 years of age: ask a doctor

Other information

store in a dry place between 65°F-75°F with pouch sealed

Inactive ingredients

citric acid, organic apple juice concentrate, organic blackberry juice concentrate, organic blueberry juice concentrate, organic cane sugar, organic cherry juice concentrate, organic cranberry juice concentrate, organic elderberry juice concentrate, organic grape juice concentrate, organic honey, organic pear juice concentrate, organic raspberry juice concentrate, organic raspberry powder, organic rice syrup, organic strawberry powder, organic watermelon flavor

Questions?

Visit our website at www.theEEZco.com, or write us at 450 Heritage Rd., Southbury, CT 06488.